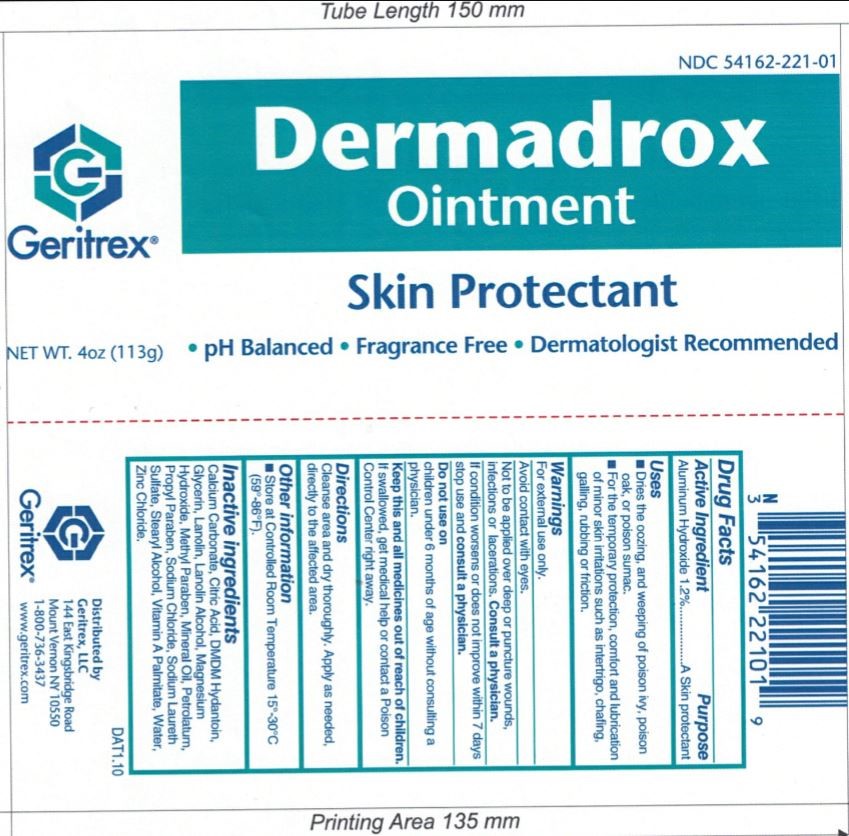 DRUG LABEL: Dermadrox
NDC: 54162-221 | Form: OINTMENT
Manufacturer: GERITREX LLC
Category: otc | Type: HUMAN OTC DRUG LABEL
Date: 20170828

ACTIVE INGREDIENTS: ALUMINUM HYDROXIDE 1.356 g/113 g
INACTIVE INGREDIENTS: CALCIUM CARBONATE; CITRIC ACID ACETATE; WATER; GLYCERIN; LANOLIN; LANOLIN ALCOHOLS; MAGNESIUM HYDROXIDE; METHYLPARABEN; PROPYLPARABEN; MINERAL OIL; PETROLATUM; SODIUM CHLORIDE; SODIUM LAURETH SULFATE; STEARYL ALCOHOL; VITAMIN A; VITAMIN D; ZINC CHLORIDE

Dermadrox Ointment

Drug Facts

Active Ingredients Purpose

Aluminum Hydroxide.............................1.2% A Skin protectant

Intended Use

Used for relief of minor skin irritations such as chafing, Interigo and galling.

Provides temporary relief to abraded skin, friction burns and rubbing.

Lubricates effectively on psoriatic skin.

Effective for dried cracked skin, sunburn and abraded skin

Directions

Apply liberally as often as necessary to minor burns, abraded skin,

irritated areas and minor wounds.

Reapply at least every 12 hours.

Warnings

For External Use Only

Avoid contact with eyes

Discontinue use if symptoms persist for more than 7 days.

DERMADROX ointment is contraindicated in patients with a

history of hypersensitivity to any of its components.

Inactive Ingredients

Calcium Carbonate, Citric acid, Deionized water, Glycerin, Lanolin, Lanolin Alcohol,

Mangnesium hydroxide, Methyl and propyl parabens, Mineral oil, Petrolatum,

Sodium chloride, Sodium laureth sulfate, Stearyl alcohol, Vitamin A and D in a

Hydrophilic ointment base, Zinc chloride.

Keep out of reach of children

STORAGE AND HANDLING

Store at room temperature (59'F-86'F).

Keep lid tightly closed.

DOSAGE AND ADMINISTRATION

Reapply at least every 12 hours